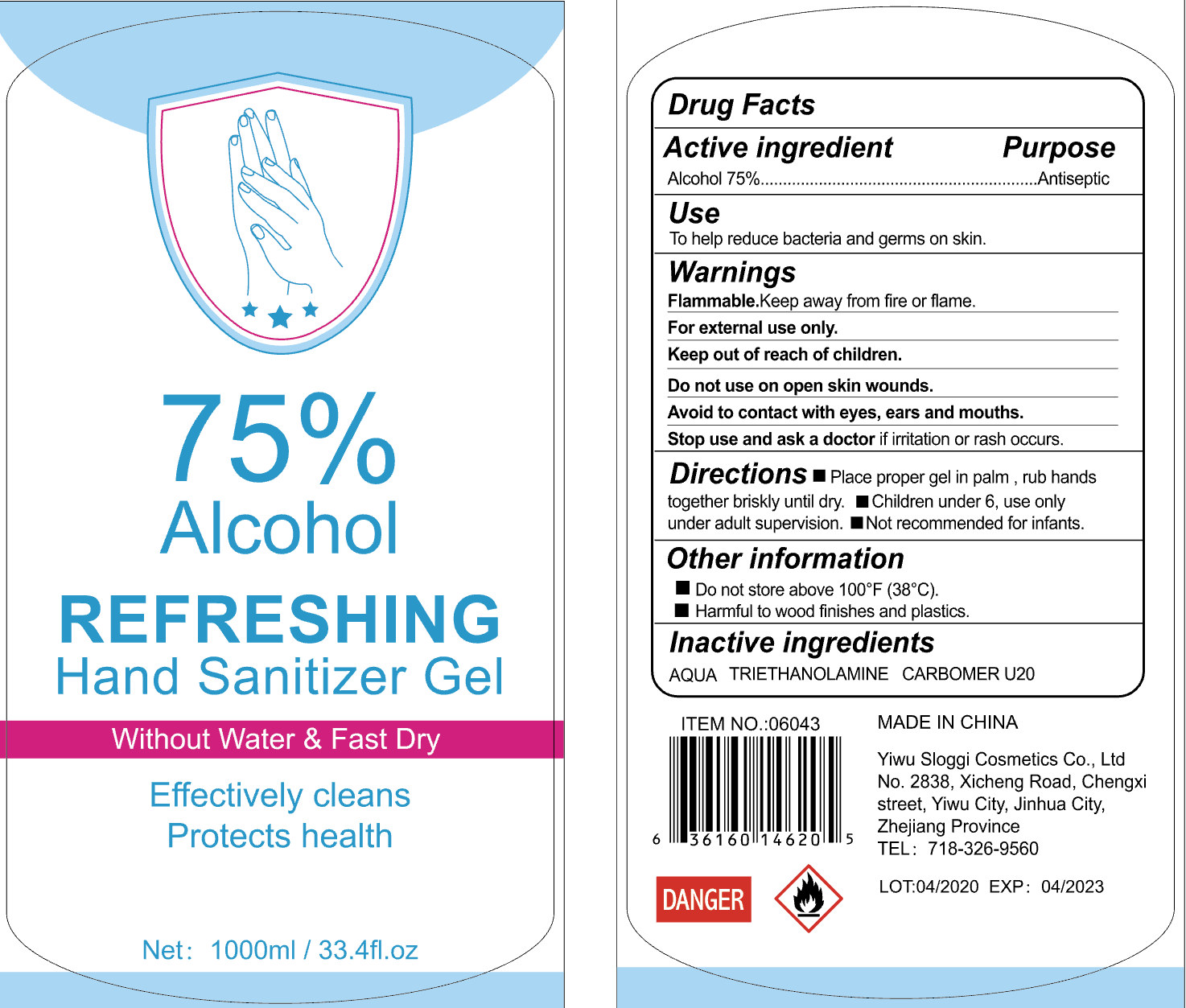 DRUG LABEL: Refreshing Hand Sanitizer Gel
NDC: 54225-010 | Form: GEL
Manufacturer: YIWU SLOGGI COSMETICS CO.,LTD
Category: otc | Type: HUMAN OTC DRUG LABEL
Date: 20200514

ACTIVE INGREDIENTS: ALCOHOL 750 mL/1000 mL
INACTIVE INGREDIENTS: PROPYLENE GLYCOL; CARBOMER HOMOPOLYMER, UNSPECIFIED TYPE; GLYCERIN; AMINOMETHYLPROPANOL; WATER

DOSAGE AND ADMINISTRATION

Store below 110 F

INACTIVE INGREDIENT

AQUA

Propylene Glycol

Glycerin

CARBOMER

AMINOMETHYL PROPANOL

INDICATIONS AND USAGE

Take appropriate amount of this productto palm and rub hands

ACTIVE INGREDIENT

ALCOHOL

keep out of reach of children

PURPOSE

Disinfection
Sterilization

WARNINGS

When using this products do not use in or near the eyes.in case of contactrinse eyes thoroughly with water.Stop use and ask a doctor if imitationor rash appears and lasts.Keep out of reach of children.if swallowed get medial help or contacta polson control center right away.